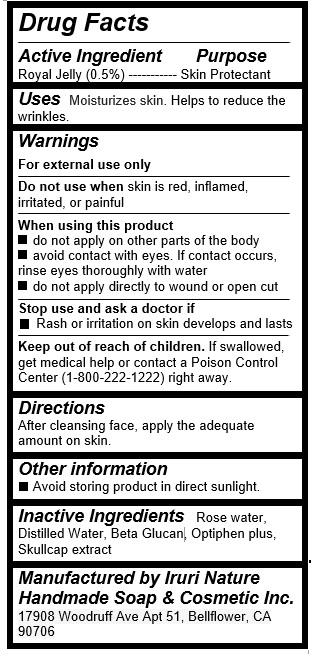 DRUG LABEL: Yellow Toner
NDC: 71547-105 | Form: LIQUID
Manufacturer: Iruri Nature Handmade Soap & Cosmetic Inc
Category: otc | Type: HUMAN OTC DRUG LABEL
Date: 20170724

ACTIVE INGREDIENTS: ROYAL JELLY 0.15 g/30 mL
INACTIVE INGREDIENTS: WATER

Yellow Toner (Rose water & Royal Jelly)

Active Ingredients

Royal Jelly (0.5%)

Purpose

Skin protectant

Uses

Moisturizes skin. Helps to reduce the wrinkles.

Warnings

For external use only

Do not use when skin is red, inflamed, irritated, or painful

When using this product

- do not apply on other parts of the body

- avoid contact with eyes. If contact occurs, rinse eyes thoroughly with water

- do not apply directly to wound or open cut

Stop use and ask a doctor if

- Rash or irritation on skin develops and lasts

Keep out of reach of children

. If swallowed, get medical help or contact a Poison Control Center (1-800-222-1222) right away.

Directions

After cleansing face, apply the adequate amount on skin.

Inactive Ingredients

Rose water, Distilled Water, Beta Glucan, Optiphen plus, Skullcap extract